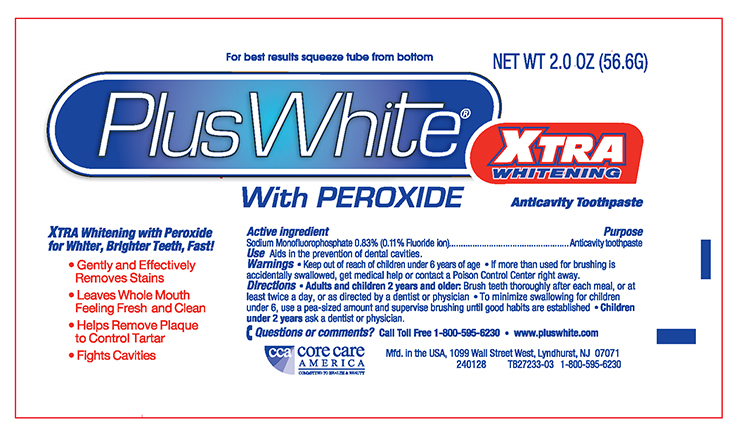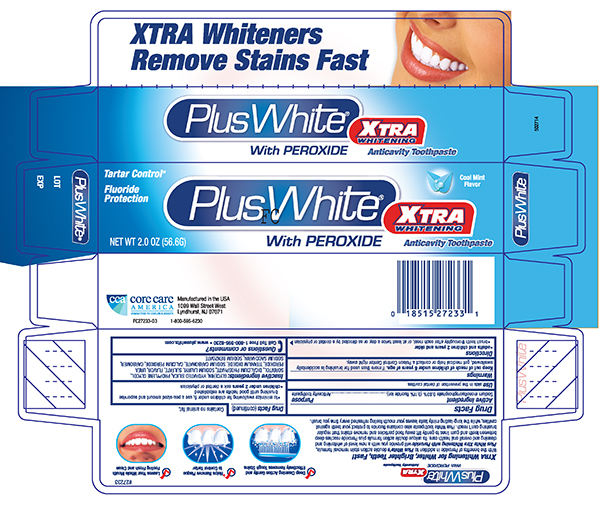 DRUG LABEL: Plus White
NDC: 61543-1751 | Form: PASTE, DENTIFRICE
Manufacturer: CCA Industries, Inc.
Category: otc | Type: HUMAN OTC DRUG LABEL
Date: 20180801

ACTIVE INGREDIENTS: SODIUM MONOFLUOROPHOSPHATE 0.83 g/100 g
INACTIVE INGREDIENTS: GLYCERIN; DIBASIC CALCIUM PHOSPHATE DIHYDRATE; HYDRATED SILICA; SODIUM LAURYL SULFATE; TITANIUM DIOXIDE; SACCHARIN SODIUM; SORBITOL; PROPYLENE GLYCOL; CARBAMIDE PEROXIDE; CARBOMER 940; SODIUM CARBONATE; CALCIUM PEROXIDE; SODIUM BENZOATE

Plus White Toothpaste with Peroxide

Active Ingredient

Sodium Monofluorophosphate 0.83% (0.11% w/v fluoride ion)

Purpose

Anticavity Toothpaste

Uses

Aids in the prevention of dental decay.

Warnings

If more than used for brushing is accidentally swallowed, get medical help or contact a Poison Control Center right away.

Directions

This toothpaste is formulated for adults 18 and over who smoke tobacco

- It should not be utilized by children under 18 years old without consulting a dentist or physician
- Brush teeth thoroughly, preferably after each meal, or at least twice a day, or when new stains are apparent.

INACTIVE INGREDIENT

Inactive ingredients: Glycerin, Hydrated Silica, Propylene Glycol, Sorbitol, Dicalcium Phosphate, Sodium Lauryl Sulfate, Flavor, Urea Peroxide, Titanium Dioxide, Sodium Carbonate, Calcium Peroxide, Carbomer, Sodium Saccharin, Sodium Benzoate

Questions or comments? Call Toll Free1-800-595-6230
- www.pluswhite.com

Principal Display Panel -Tube 2.0 oz

Plus+White
Plus White TOOTHPASTE with Peroxide
Net Wt 2.0 oz (56.6G) - Fluoride Anticavity Toothpaste

Principal Display Panel - Carton 2.0 oz

Plus + White

Plus White Toothpaste with Peroxide

NET WT 2.0 oz (56.6G) Fluoride Anticavity Toothpaste